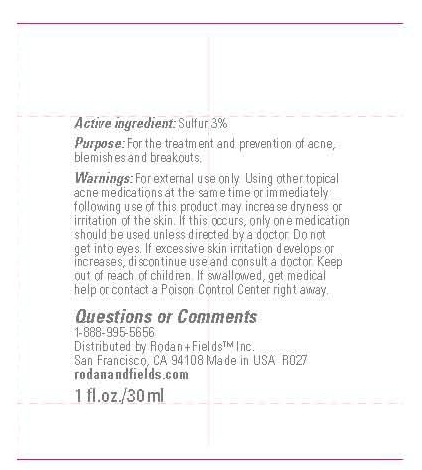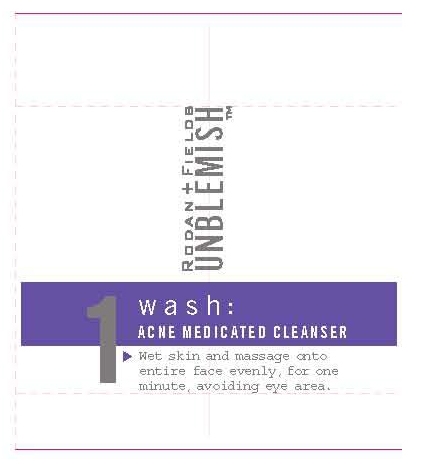 DRUG LABEL: Rodan and Fields
NDC: 56152-2050 | Form: CREAM
Manufacturer: Cosmetic Enterprises Ltd. 
Category: otc | Type: HUMAN OTC DRUG LABEL
Date: 20100624

ACTIVE INGREDIENTS: SULFUR 3 mL/100 mL

1 Wash Acne Medicated Cleanser

Active Ingredients

Sulfur 3%

WARNINGS

Warnings: For external use only. Using other topical acne medications at the same time or immediately following use of this product may increase dryness or irritation of the skin. If this occurs, only one medication should be used unless directed by a doctor. Do not get into eyes. If excessive skin irritation develops or increases, discontinue use and consult a doctor. Keep out of reach of children. If swallowed, get medical help or contact a Poison Control Center right away.

INDICATIONS AND USAGE

Purpose: For the treatment and prevention of acne, blemishes and breakouts.

Questions or Comments
1-888-955-5656

PACKAGE LABEL

Wash

1 fl. oz./30 mL